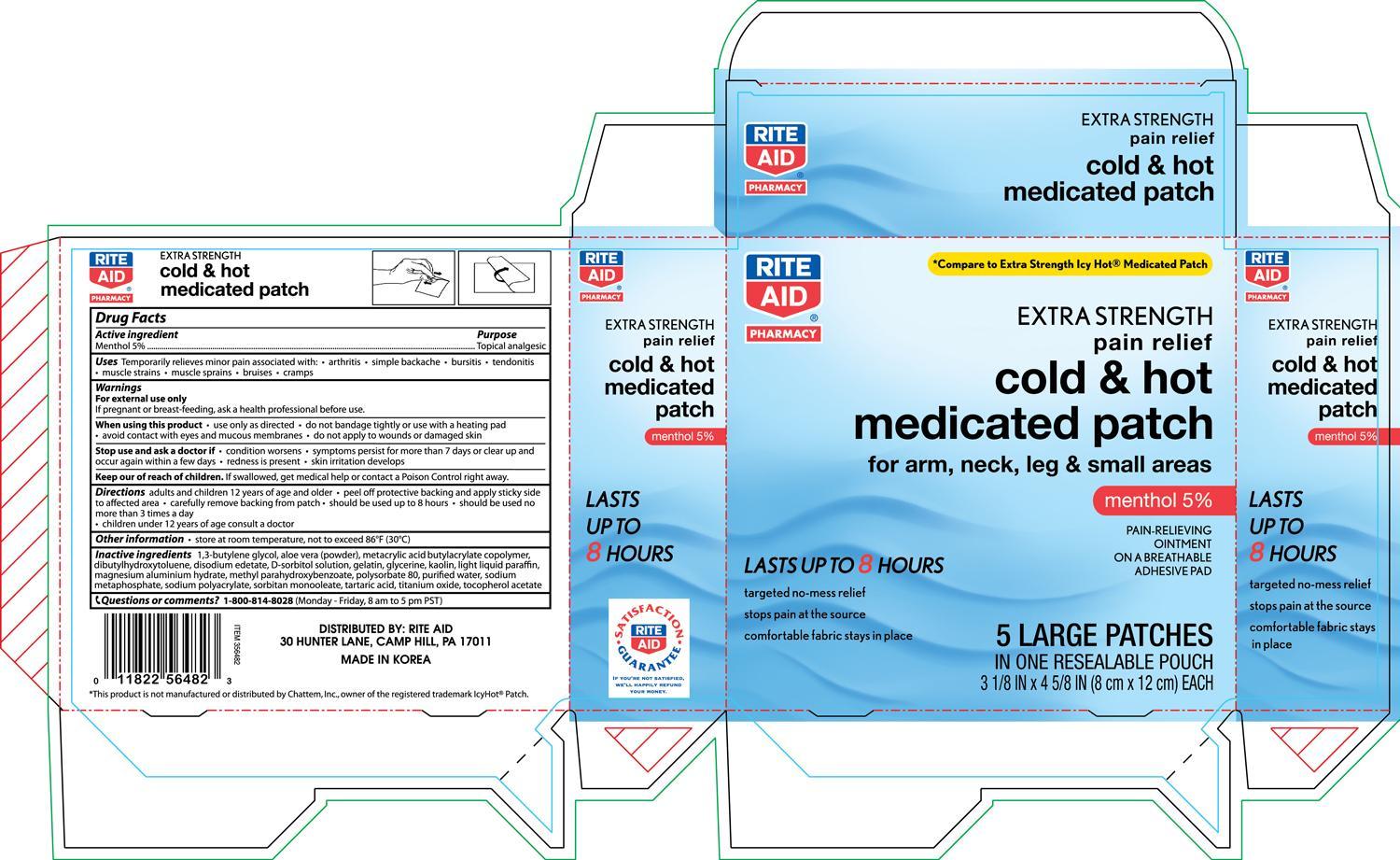 DRUG LABEL: Rite Aid Extra Strength Pain Relief Cold and Hot Medicated
NDC: 11822-5649 | Form: PATCH
Manufacturer: Rite Aid
Category: otc | Type: HUMAN OTC DRUG LABEL
Date: 20130630

ACTIVE INGREDIENTS: MENTHOL 750 mg/1 1
INACTIVE INGREDIENTS: BUTYLENE GLYCOL; ALOE VERA LEAF; EDETATE DISODIUM; GELATIN; GLYCERIN; KAOLIN; LIGHT MINERAL OIL; METHYLPARABEN; POLYSORBATE 80; WATER; SODIUM POLYMETAPHOSPHATE; SORBITAN MONOOLEATE; TARTARIC ACID; TITANIUM DIOXIDE; ALPHA-TOCOPHEROL ACETATE

Drug Facts

Active ingredient Purpose

Menthol 5%................................................................Topical analgesic

PURPOSE

Uses Temporarily relieves minor pain associated with:

- arthritis
- simple backache
- bursitis
- tendonitis
- muscle strains
- muscle sprains
- bruises
- cramps

Warnings For external use only

When using this product

- use only as directed
- do not bandage tightly or use with a heating pad
- avoid contact with eyes and mucous membranes
- do not apply to wounds or damaged skin

Stop use and ask a doctor if

- condition worsens
- symptoms persist for more than 7 days or clear up and occur again within a few days
- redness is present
- skin irritation develops

Keep out of reach of children. If swallowed, get medical help or contact a Poison Control Center right away.

PREGNANCY OR BREAST FEEDING

If pregnant or breast-feeding, ask a health professional before use.

Directions

- adults and children 12 years of age and older
- peel off protective backing and apply sticky side to affected area
- carefully remove backing from patch
- should be used up to 8 hours
- should be used no more than 3 times a day
- children under 12 years or age consult a doctor

Other information

- store at room temperature, not to exceed 86°F (30°C)

INACTIVE INGREDIENT

Inactive ingredients 1,3-butylene glycol, aloe vera (powder), metacrylic acid butylacrylic acid butylacrylate copolymer, dibutylhydroxytoluene, disodium edetate, D-sorbitol solution, gelatin, glycerine, kaolin, light liquid paraffin, magnesium aluminium hydrate, methyl parahydroxybenzoate, polysorbate 80, purified water, sodium metaphosphate, sodium polyacrylate, sorbitan monooleate, tartaric acid, titanium oxide, tocopherol acetate.

DOSAGE AND ADMINISTRATION

Distributed By:

Rite Aid

30 Hunter Lane

Camp Hill, PA 17011

Made in Korea